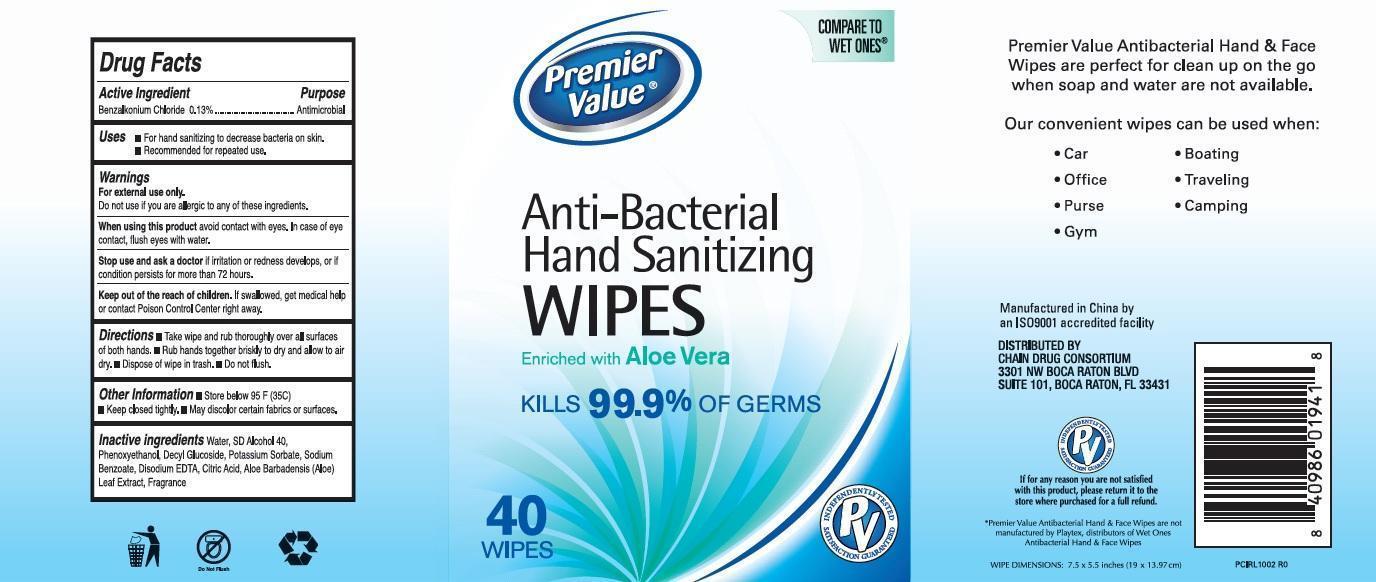 DRUG LABEL: Premier Value Antibacterial Hand sanitizingenriched with ALO
NDC: 68016-112 | Form: CLOTH
Manufacturer: Premier Value (Chain Drug Consortium, LLC)
Category: otc | Type: HUMAN OTC DRUG LABEL
Date: 20130716

ACTIVE INGREDIENTS: BENZALKONIUM CHLORIDE 0.13 g/100 g
INACTIVE INGREDIENTS: WATER; PHENOXYETHANOL; DECYL GLUCOSIDE; POTASSIUM SORBATE; SODIUM BENZOATE; EDETATE DISODIUM; CITRIC ACID MONOHYDRATE; ALOE VERA LEAF

Drug Facts

Active Ingredient

Benzalkonium Chloride 0.13%

Purpose

Antimicrobial

Uses

- For hand sanitizing to decrease bacteria on skin.
- Recommended for repeated use.

Warnings

For external use only.

Do not use if you are allergic to any of these ingredients.

When using this product

avoid contact with eyes. In case of eye contact, flush eyes with water.

Stop use and ask a doctor

if irritation or redness develops, or if condition persists for more than 72 hours.

Keep out of reach of children.

If swallowed , get medical help or contact Poison Control Center right away.

Directions

- Take wipe and rub throughly over all surfaces of both hands
- Rub hands together briskly to dry and allow to air dry.
- Dispose of wipe in trash
- Do not flush.

Other Information

- Store below 95 F(35C)
- Keep closed tightly
- May discolor certain fabrics or surfaces.

Inactive ingredients

Water, SD Alcohol 40, Phenoxyethanol, Decyl Glucoside, Potassium Sorbate, Sodium Benzoate, Disodium EDTA, Citric Acid, Aloe Barbadensis (Aloe) Leaf Extract, Fragrance

Principal Display Panel

COMPARED TO

WET ONES

Premier Value

Anti-Bacterial

Hand Sanitizing

KILLS 99.9% OF GERMS

WIPES

Enriched with Aloe Vera

40 Wipes